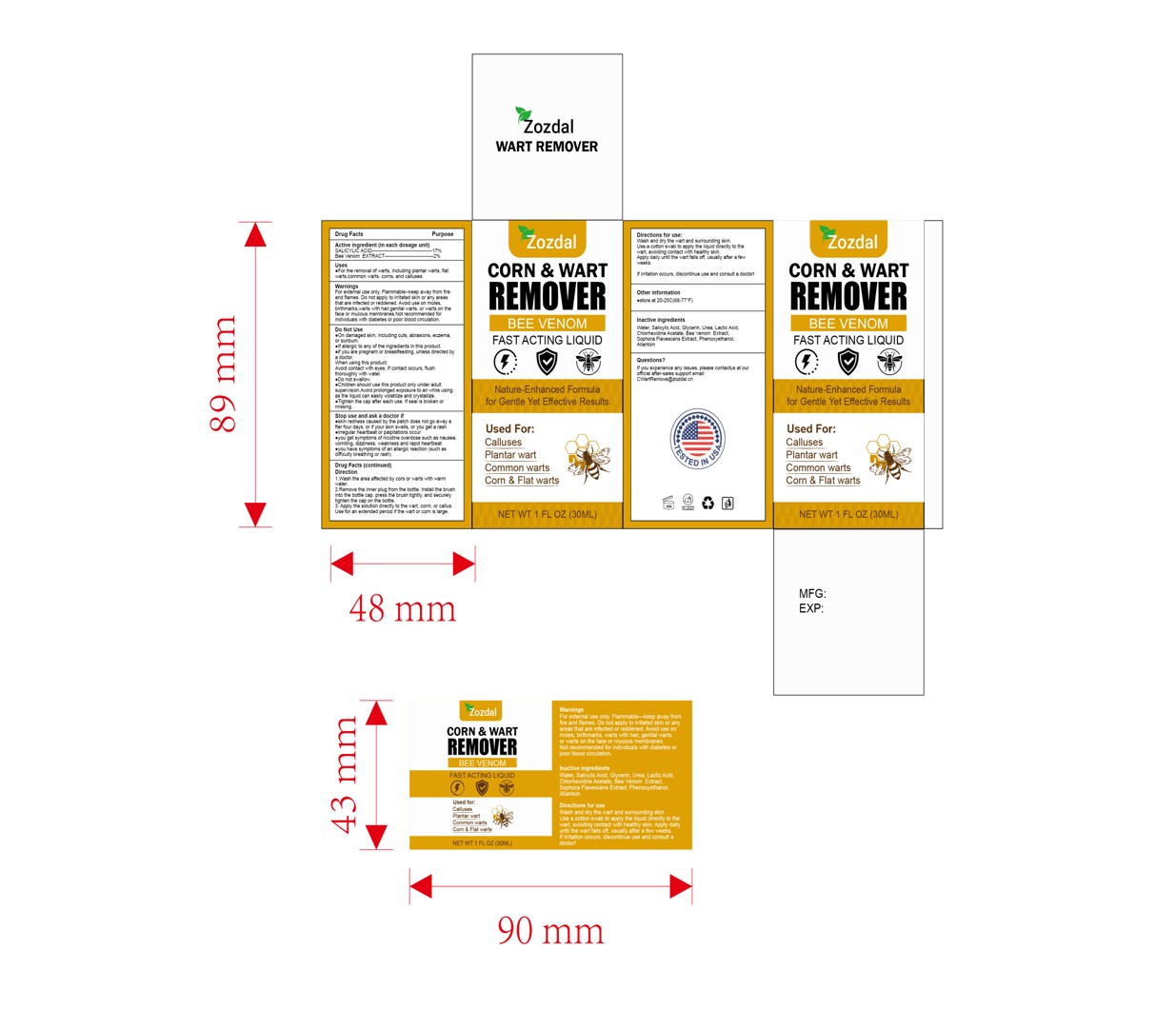 DRUG LABEL: Vryioh Wart Remover
NDC: 84867-016 | Form: LIQUID
Manufacturer: Jiashen International Trade Limited
Category: otc | Type: HUMAN OTC DRUG LABEL
Date: 20250717

ACTIVE INGREDIENTS: APIS MELLIFERA VENOM 2 g/100 mL; SALICYLIC ACID 17 g/100 mL
INACTIVE INGREDIENTS: ALLANTOIN; CHLORHEXIDINE ACETATE; HYDROXYETHYLCELLULOSE; UREA; GLYCERIN; PHENOXYETHANOL; AQUA; LACTIC ACID; SOPHORA FLAVESCENS ROOT

ACTIVE INGREDIENT

Bee Venom 2%
Salicylic Acid 17%

PURPOSE

wart, corn and callus remover

KEEP OUT OF REACH OF CHILDREN

Please keep the product out of reach of children. If accidentally ingested, please call the emergency center immediately.

WARNINGS

WarningsFor external use only. Flammable-keep away from fireand flames. Do not apply to irritated skin or any areasthat are infected or reddened. Avoid use on moles,birthmarks,warts with hair,genital warts, or warts on theface or mucous membranes.Not recommended forindividuals with diabetes or poor blood circulation.

Stop use and ask a doctor ifeskin redness caused by the patch does not go away after four days, or if your skin swells, or you get a rasheiregular heartbeat or palpitations occureyou get symptoms of nicotine overdose such as nausea.vomiting,dizziness, weakness and rapid heartbeateyou have symptoms of an allergic reaction (such asdifficulty breathing or rash)

DOSAGE AND ADMINISTRATION

Apply the solution directly to the wart, corm, or callus.Use for an extended period if the wart or corn is large.

INDICATIONS AND USAGE

Direction
1.Wash the area affected by cors or warts with warmwater.2.Remove the inner plug from the bottle. Instail the brushinto the bottle cap. press the brush tightly, and securelytighten the cap on the bottle.3. Apply the solution directly to the wart, corm, or callus.Use for an extended period if the wart or corn is large.

INACTIVE INGREDIENT

AQUA
GLYCERIN
LACTIC ACID
UREA
Chlorhexidine Acetate
SOPHORA FLAVESCENS EXTRACT
HYDROXYETHYLCELLULOSE
ALLANTOIN
PHENOXYETHANOL